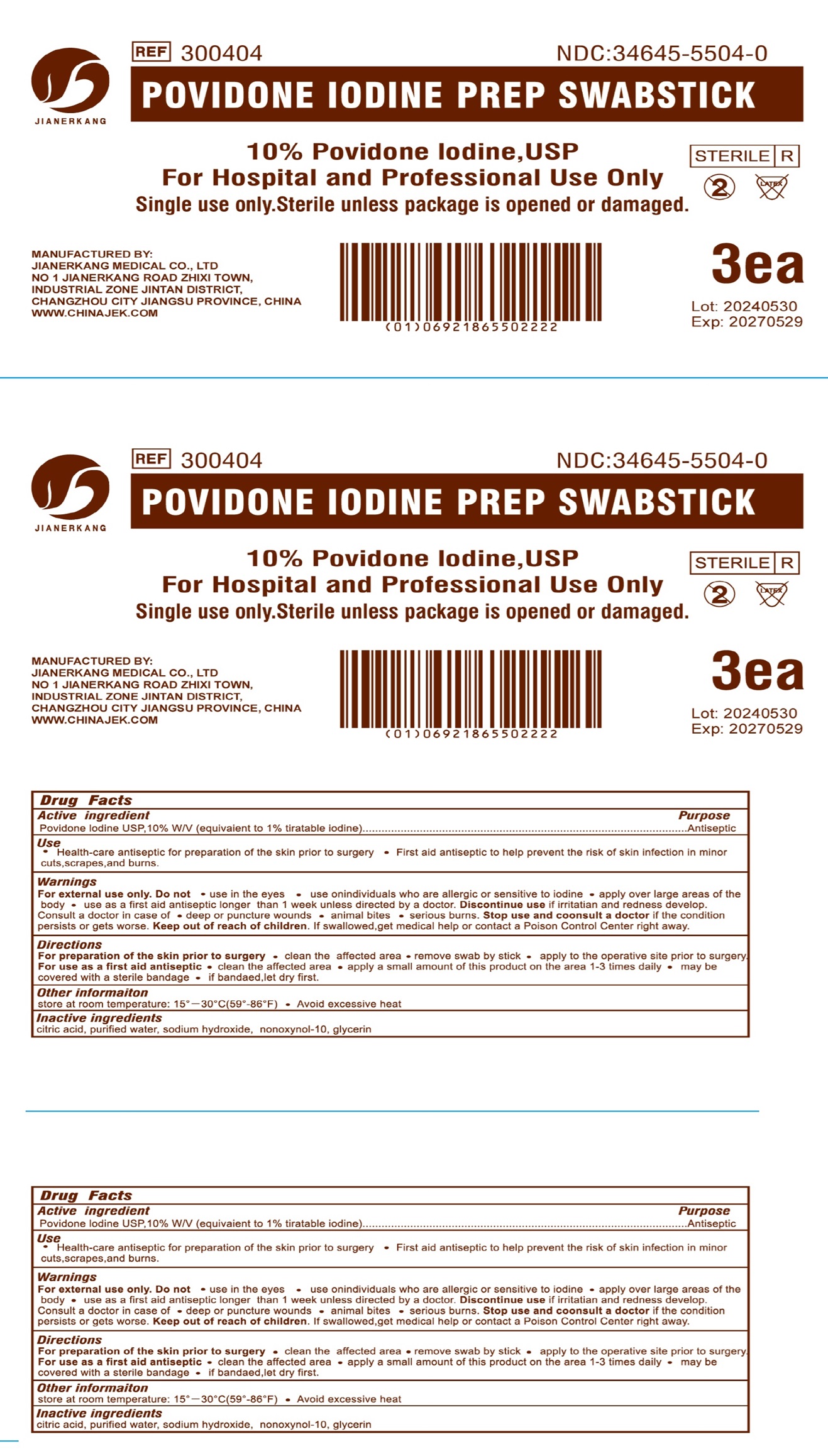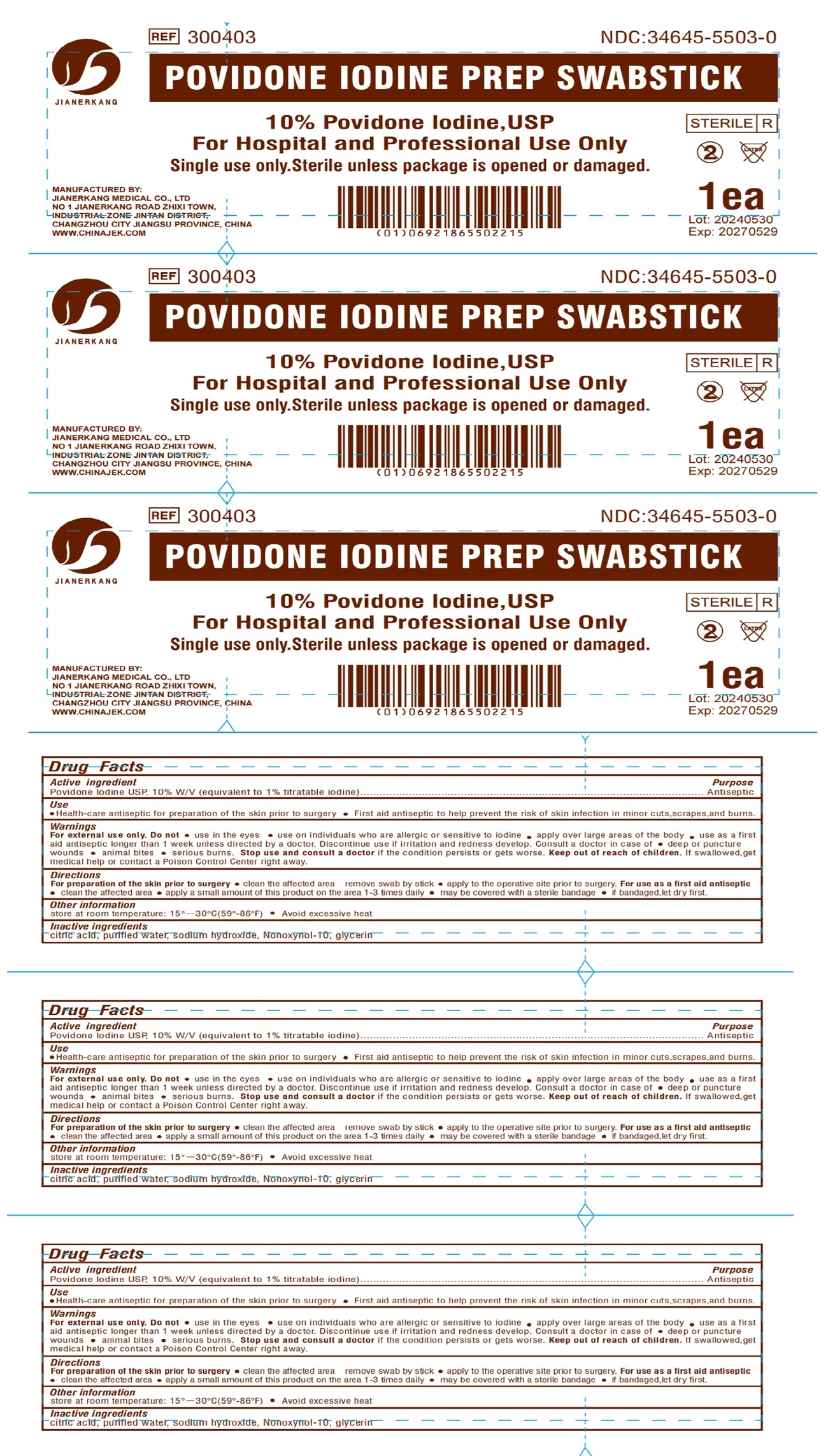 DRUG LABEL: Povidone Iodine Prep
NDC: 34645-5506 | Form: SWAB
Manufacturer: Jianerkang Medical Co., Ltd
Category: otc | Type: HUMAN OTC DRUG LABEL
Date: 20240911

ACTIVE INGREDIENTS: POVIDONE-IODINE 100 mg/1 g
INACTIVE INGREDIENTS: CITRIC ACID MONOHYDRATE; WATER; SODIUM HYDROXIDE; NONOXYNOL-10; GLYCERIN

Povidone Iodine Prep Swabstick

Active ingredient

Povidone Iodine USP, 10% W/V (equivalent to 1% titratable iodine)

Purpose

Antiseptic

Use

- Health-care antiseptic for preparation of the skin prior to surgery
- First aid antiseptic to help prevent the risk of skin infection in minor cuts,scrapes,and burns.

Warnings

For external use only.

Do not

- use in the eyes
- use on individuals who are allergic or sensitive to iodine
- apply over large areas of the body
- use as a first aid antiseptic longer than 1 week unless directed by a doctor. Discontinue use if irritation and irritation and redness develop. Consult a doctor in case of
- deep or puncture wounds
- animal bites
- serious burns.

Stop use and consult a doctor

if the condition persists or gets worse.

Keep out of reach of children.

If swallowed, get medical help or contact a Poison Control Center right away.

Directions

For preparation of the skin prior to surgery

- clean the affected area remove swab by stick
- apply to the operative site prior to surgery.

For use as a first aid antiseptic

- clean the affected area
- apply a small amount of this product on the area 1-3 times daily
- may be covered with a sterile bandage
- if bandaged,let dry first.

Other information

store at room temperature: 15°—30°C(59°-86°F)

- Avoid excessive heat

Inactive ingredients

citric acid, purified water, sodium hydroxide, Nonoxynol - 10, glycerin